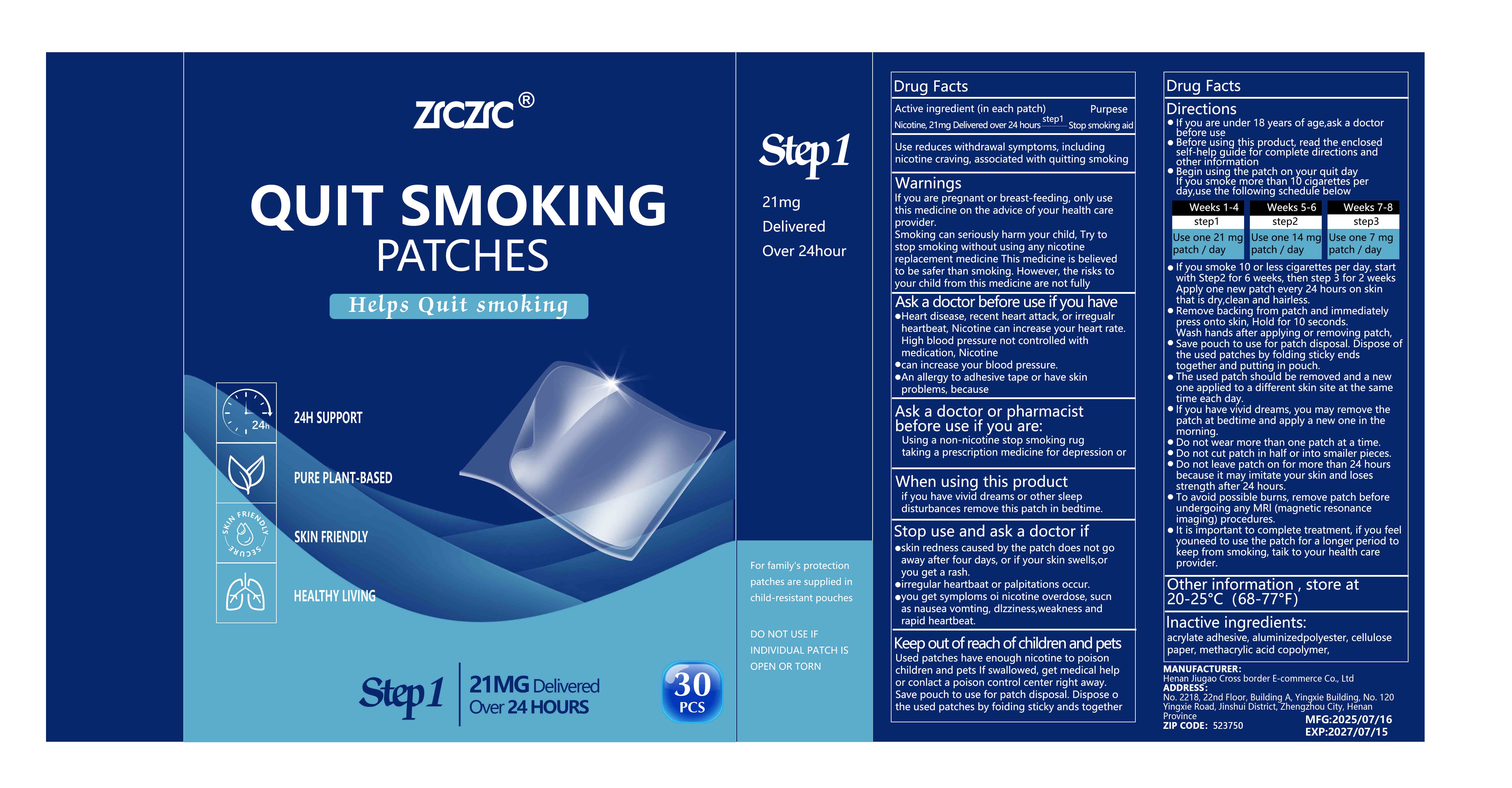 DRUG LABEL: quit smoking patches
NDC: 87135-001 | Form: PATCH
Manufacturer: Henan Jiugao Cross-border Ecommerce Co., Ltd.
Category: otc | Type: HUMAN OTC DRUG LABEL
Date: 20251008

ACTIVE INGREDIENTS: NICOTINE 21 mg/1 1
INACTIVE INGREDIENTS: METHACRYLIC ACID - METHYL METHACRYLATE COPOLYMER (1:1)

87135-001 quit smoking patches

ACTIVE INGREDIENT

nicotine

PURPOSE

Stop smoking aid

INDICATIONS AND USAGE

Use reduces withdrawal symptoms, includingnicotine craving, associated with quittingsmoking

WARNINGS

lf you are pregnant or breast-feeding, only usethis medicine on the advice of your health careproviderSmoking can seriously harm your child, Try tostop smoking without using any nicotinereplacement medicine This medicine is believedto be safer than smoking. However, the risks toyour child from this medicine are not fullyknown.

Ask a doctor before use if you havee
Heart disease, recent heart attack, or irregualr heartbeat, Nicotine can increase your heart rate.
High blood pressure not controlled withmedication, Nicotine
can increase your blood pressure.
An allergy to adhesive tape or have skinproblems, because you are more likely to get rashes.
Ask a doctor or pharmacist before use if you are:
Using a non-nicotine stop smoking rug taking a prescription medicine for depression or asthma.Your prescription dose may need to be adjusted

When using this product Stop use and ask a doctor if
if you have vivid dreams or other sleep disturbances remove this patch in bedtime

Keep out of reach of children and pets
Used patches have enough nicotine to poisonchildren and pets if swallowed, get medicalhelp or conlact a poison control center rightaway. Save pouch to use for patch disposal.Dispose o the used patches by foiding sticky ands together and putung in pouch.

Directions
lf you are under 18 years of age,ask a doctor before use
Before using this product, read the enclosedself-help guide for complete directions andother information
Begin using the patch on your quit dayIf you smoke more than 10 cigarettes perday,use the following schedule below
Weeks 1-4
step1 Use one 21 mgpatch / day
Weeks 5-6
step2 Use one 14 mg patch / day
Weeks 7-8
step3 Use one 7 mgpatch / day
lf you smoke 10 or less cigarettes per day,start with Step2 for 6 weeks, then step 3 for2 weeks Apply one new patch every 24 hourson skin that is dry,clean and hairless.Remove backing from patch andimmediately press onto skin, Hold for 10seconds.Wash hands after applying orremoving patch,Save pouch to use for patch disposal.Dispose of the used patches by folding stickyends together and putting in pouch.The used patch should be removed and anew one applied to a different skin site atthe same time each day.if you have vivid dreams, you may removethe patch at bedtime and apply a new one inthe morning.
Do not wear more than one patch at a time.Do not cut patch in half or into smailerpieces.Do not leave patch on for more than 24hours because it may imitate your skin andloses strength after 24 hours.To avoid p¶ssible burns, remove patchbefore undergoing any MRl (magneticresonance imaging)procedures.It is important to complete treatment, if youfeel youneed to use the patch for a longerperiod to keep from smoking, taik to yourhealth care provider.

INACTIVE INGREDIENT

methacrylic acid copolymer